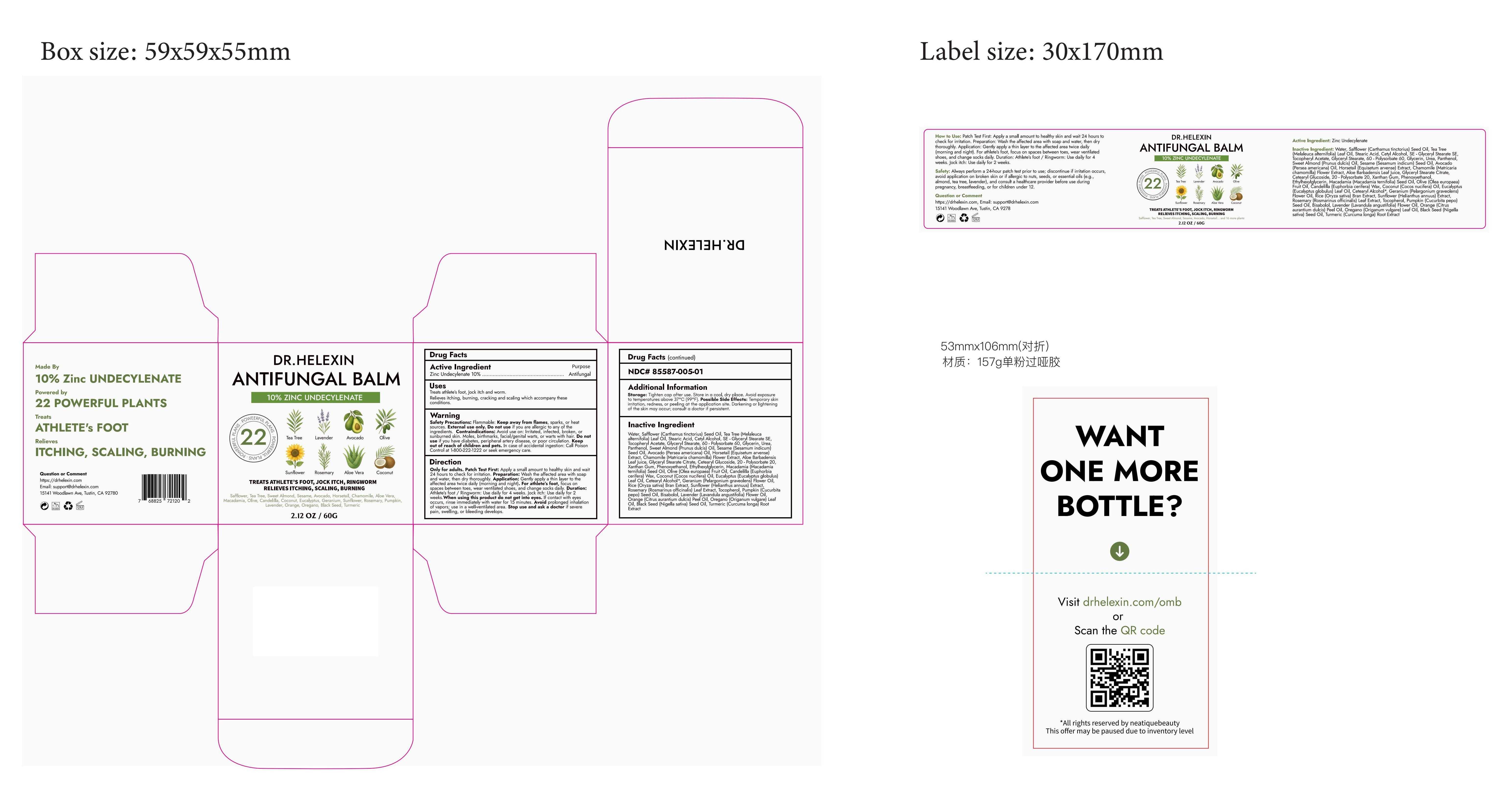 DRUG LABEL: Dr. Helexin Antifungal Balm
NDC: 85587-005 | Form: CREAM
Manufacturer: Shenzhen Zealous Ecommerce Technology Co., Ltd
Category: otc | Type: HUMAN OTC DRUG LABEL
Date: 20250729

ACTIVE INGREDIENTS: ZINC UNDECYLENATE 10 g/100 g
INACTIVE INGREDIENTS: UREA; PANTHENOL; ALOE VERA LEAF JUICE; ETHYLHEXYLGLYCERIN; COCOS NUCIFERA (COCONUT) OIL; PELARGONIUM GRAVEOLENS LEAF OIL; TOCOPHEROL; CHAMOMILE; CITRUS AURANTIUM DULCIS (ORANGE) PEEL OIL; ORIGANUM VULGARE LEAF OIL; XANTHAN GUM; NIGELLA SATIVA SEED OIL; MELALEUCA ALTERNIFOLIA (TEA TREE) LEAF OIL; CETYL ALCOHOL; .ALPHA.-TOCOPHEROL ACETATE; POLYSORBATE 20; CUCURBITA PEPO (PUMPKIN) SEED OIL; EQUISETUM ARVENSE TOP; EUCALYPTUS GLOBULUS LEAF OIL; WATER; BISABOLOL; LAVENDER OIL; SESAMUM INDICUM (SESAME) SEED OIL; POLYSORBATE 60; EUPHORBIA CERIFERA (CANDELILLA) WAX; PRUNUS AMYGDALUS DULCIS (SWEET ALMOND) OIL; HYDROGENATED MACADAMIA SEED OIL; SAFFLOWER OIL; PHENOXYETHANOL; OLEA EUROPAEA (OLIVE) FRUIT OIL; STEARIC ACID; GLYCERYL STEARATE SE; GLYCERIN; PERSEA GRATISSIMA (AVOCADO) OIL; ROSMARINUS OFFICINALIS (ROSEMARY) LEAF OIL; CURCUMA LONGA (TURMERIC) ROOT

85587-005

Active Ingredient

Zinc Undecylenate 10%

Purpose

Treats athlete’s foot, Jock itch and worm, Relieves itching, burning, cracking and scaling which accompany these conditions.

Use

Apply a small amount to healthy skin and wait 24 hours to check for irritation

Warnings

Always perform a 24-hour patch test prior to use; discontinue if irritation occurs, avoid application on broken skin or if allergic to nuts, seeds, or essential oils (e.g., almond, tea tree, lavender), and consult a healthcare provider before use during pregnancy, breastfeeding, or for children under 12.

Do not use

Avoid application on broken skin or if allergic to nuts, seeds, or essential oils

When Using

Wash the affected area with soap and water, then dry thoroughly.

Stop Use

Discontinue if irritation occurs

Ask Doctor

Consult a healthcare provider before use during pregnancy, breastfeeding, or for children under 12.

Keep Out Of Reach Of Children

Directions

Gently apply a thin layer to the affected area twice daily (morning and night).

Inactive ingredients

Water，Safflower (Carthamus tinctorius) Seed Oil, Tea Tree (Melaleuca alternifolia) Leaf Oil, Stearic Acid, Cetyl Alcohol, SE - Glyceryl Stearate SE, Tocopheryl Acetate, Glyceryl Stearate, 60 - Polysorbate 60, Glycerin, Urea, Panthenol, Sweet Almond (Prunus dulcis) Oil, Sesame (Sesamum indicum) Seed Oil, Avocado (Persea americana) Oil, Horsetail (Equisetum arvense) Extract, Chamomile (Matricaria chamomilla) Flower Extract, Aloe Barbadensis Leaf Juice, Glyceryl Stearate Citrate, Cetearyl Glucoside, 20 - Polysorbate 20, Xanthan Gum, Phenoxyethanol, Ethylhexylglycerin, Macadamia (Macadamia ternifolia) Seed Oil, Olive (Olea europaea) Fruit Oil, Candelilla (Euphorbia cerifera) Wax, Coconut (Cocos nucifera) Oil, Eucalyptus (Eucalyptus globulus) Leaf Oil, Cetearyl Alcohol*, Geranium (Pelargonium graveolens) Flower Oil, Rice (Oryza sativa) Bran Extract, Sunflower (Helianthus annuus) Extract, Rosemary (Rosmarinus officinalis) Leaf Extract, Tocopherol, Pumpkin (Cucurbita pepo) Seed Oil, Bisabolol, Lavender (Lavandula angustifolia) Flower Oil, Orange (Citrus aurantium dulcis) Peel Oil, Oregano (Origanum vulgare) Leaf Oil, Black Seed (Nigella sativa) Seed Oil, Turmeric (Curcuma longa) Root Extract

Questions

https://drhelexin.com

Email: support@drhelexin.com